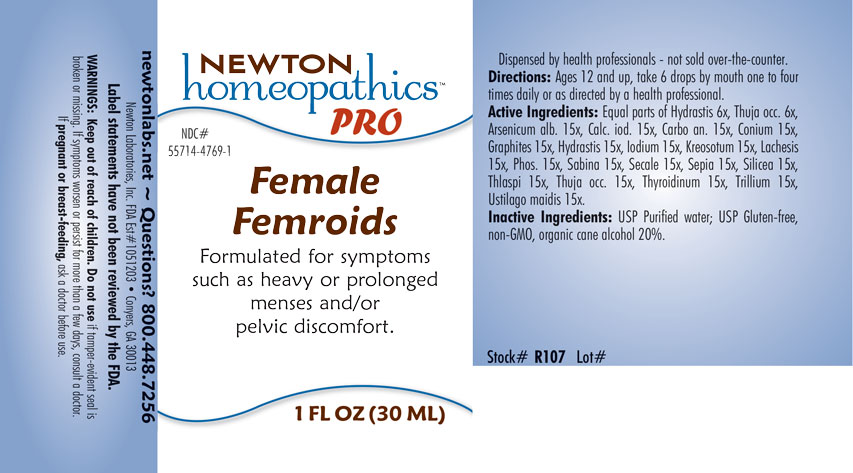 DRUG LABEL: Female Femroids
NDC: 55714-4769 | Form: LIQUID
Manufacturer: Newton Laboratories, Inc.
Category: homeopathic | Type: HUMAN OTC DRUG LABEL
Date: 20201203

ACTIVE INGREDIENTS: GOLDENSEAL 15 [hp_X]/1 mL; USTILAGO MAYDIS 15 [hp_X]/1 mL; ARSENIC TRIOXIDE 15 [hp_X]/1 mL; CALCIUM IODIDE 15 [hp_X]/1 mL; CARBO ANIMALIS 15 [hp_X]/1 mL; CONIUM MACULATUM FLOWERING TOP 15 [hp_X]/1 mL; GRAPHITE 15 [hp_X]/1 mL; IODINE 15 [hp_X]/1 mL; WOOD CREOSOTE 15 [hp_X]/1 mL; LACHESIS MUTA VENOM 15 [hp_X]/1 mL; PHOSPHORUS 15 [hp_X]/1 mL; JUNIPERUS SABINA LEAFY TWIG 15 [hp_X]/1 mL; CLAVICEPS PURPUREA SCLEROTIUM 15 [hp_X]/1 mL; SEPIA OFFICINALIS JUICE 15 [hp_X]/1 mL; SILICON DIOXIDE 15 [hp_X]/1 mL; CAPSELLA BURSA-PASTORIS 15 [hp_X]/1 mL; THUJA OCCIDENTALIS LEAFY TWIG 15 [hp_X]/1 mL; THYROID, UNSPECIFIED 15 [hp_X]/1 mL; TRILLIUM ERECTUM ROOT 15 [hp_X]/1 mL
INACTIVE INGREDIENTS: WATER; ALCOHOL

Female 4769L

INDICATIONS & USAGE SECTION

Formulated for symptoms such as heavy or prolonged menses and/or pelvic discomfort.

DOSAGE & ADMINISTRATION SECTION

Directions: Ages 12 and up, take 6 drops by mouth one to four times daily or as directed by a health professional

OTC - ACTIVE INGREDIENT SECTION

Equal parts of Hydrastis canadensis 6x, Thuja occidentalis 6x, Arsenicum album 15x, Calcarea iodata 15x, Carbo animalis 15x, Conium maculatum 15x, Graphites 15x, Hydrastis canadensis 15x, Iodium 15x, Kreosotum 15x, Lachesis mutus 15x, Phosphorus 15x, Sabina 15x, Secale cornutum 15x, Sepia 15x, Silicea 15x, Thlaspi bursa-pastoris 15x, Thuja occidentalis 15x, Thyroidinum 15x, Trillium pendulum 15x, Ustilago maidis 1

OTC - PURPOSE SECTION

Formulated for symptoms such as heavy or prolonged menses and/or pelvic discomfort.

INACTIVE INGREDIENT SECTION

Inactive Ingredients: USP Purified Water; USP Gluten-free, non-GMO, organic cane alcohol 20%.

QUESTIONS SECTION

newtonlabs.net - Questions? 800.448.7256

Newton Laboratories, Inc. FDA Est # 1051203 Conyers, GA 30013

WARNINGS SECTION

WARNINGS: Keep out of reach of children. Do not use if tamper-evident seal is broken or missing. If symptoms worsen or persist for more than a few days, consult a doctor. If pregnant or breast-feeding, ask a doctor before use.

OTC - PREGNANCY OR BREAST FEEDING SECTION

If pregnant or breast-feeding, ask a doctor before use.

OTC - KEEP OUT OF REACH OF CHILDREN SECTION

Keep out of reach of children.